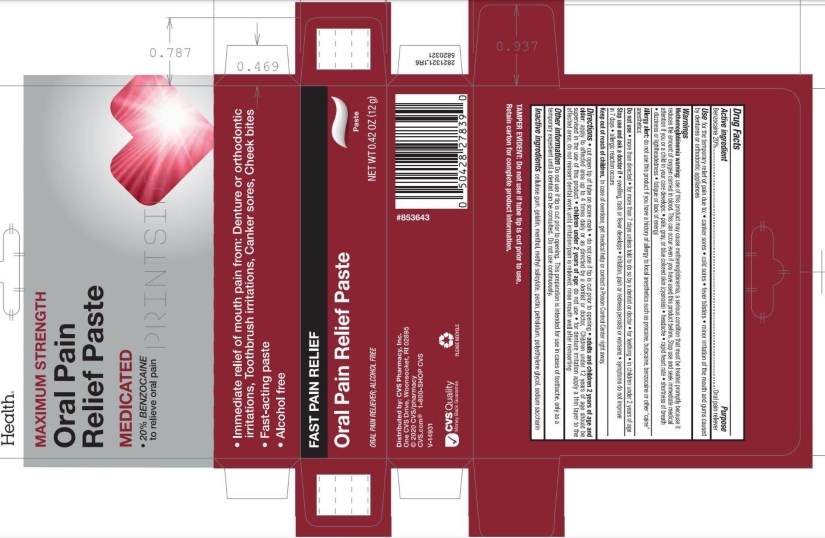 DRUG LABEL: CVS
NDC: 59779-123 | Form: PASTE, DENTIFRICE
Manufacturer: CVS Pharmacy
Category: otc | Type: HUMAN OTC DRUG LABEL
Date: 20250120

ACTIVE INGREDIENTS: BENZOCAINE 20 g/100 g
INACTIVE INGREDIENTS: MENTHOL; PETROLATUM; GELATIN; POLYETHYLENE GLYCOL 1000; SACCHARIN; METHYL SALICYLATE; PECTIN; CARBOXYMETHYLCELLULOSE SODIUM

5820321 CVS Max Str Oral Pain Reliever Paste

Active ingredient

Benzocaine 20%

Purpose

Oral pain reliever

Use

for the temporary relief of pain due to

- canker sores
- cold sores
- fever blisters
- minor irritation of the mouth and gums caused by dentures or orthodontic appliances

Warnings

Allergy alert: do not use this product if you have a history of allergy to local anesthetics such as procaine, butacaine, benzocaine or other “caine” anesthetics

When using this product

- avoid contact with the eyes
- do not use more than directed
- do not use for more than 7 days unless directed by a dentist or doctor.

Stop use and ask a doctor if

- sore mouth symptoms do not improve in 7 days
- swelling, rash or fever develops
- irritation, pain or redness persists or worsens

Keep out of reach of children. In case of overdose, get medical help or contact a Poison Control Center right away.

Directions

- cut open tip of tube on scoremark
- adults and children 2 years of age and older: apply to the affected area up to 4 times daily or as directed by a dentist or doctor. Children under 12 years of age should be supervised in the use of this product.
- children under 2 years of age: ask a dentist or doctor.
- for denture irritation apply a thin layer to the affected area; do not reinsert dental work until irritation/pain is relieved; rinse mouth well after reinserting

Other Information

Do not use if tip is cut prior to opening. This preparation is intended for use in cases of toothache, only as a tempory expedient until a dentist can be consulted. Do not use continuously. This formula will stay in place for extended duration of relief.

Inactive ingredients

Cellulose Gum, Gelatin, Menthol, Methyl Salicylate, Pectin, Petrolatum, Polyethylene Glycol, Sodium Saccharin.